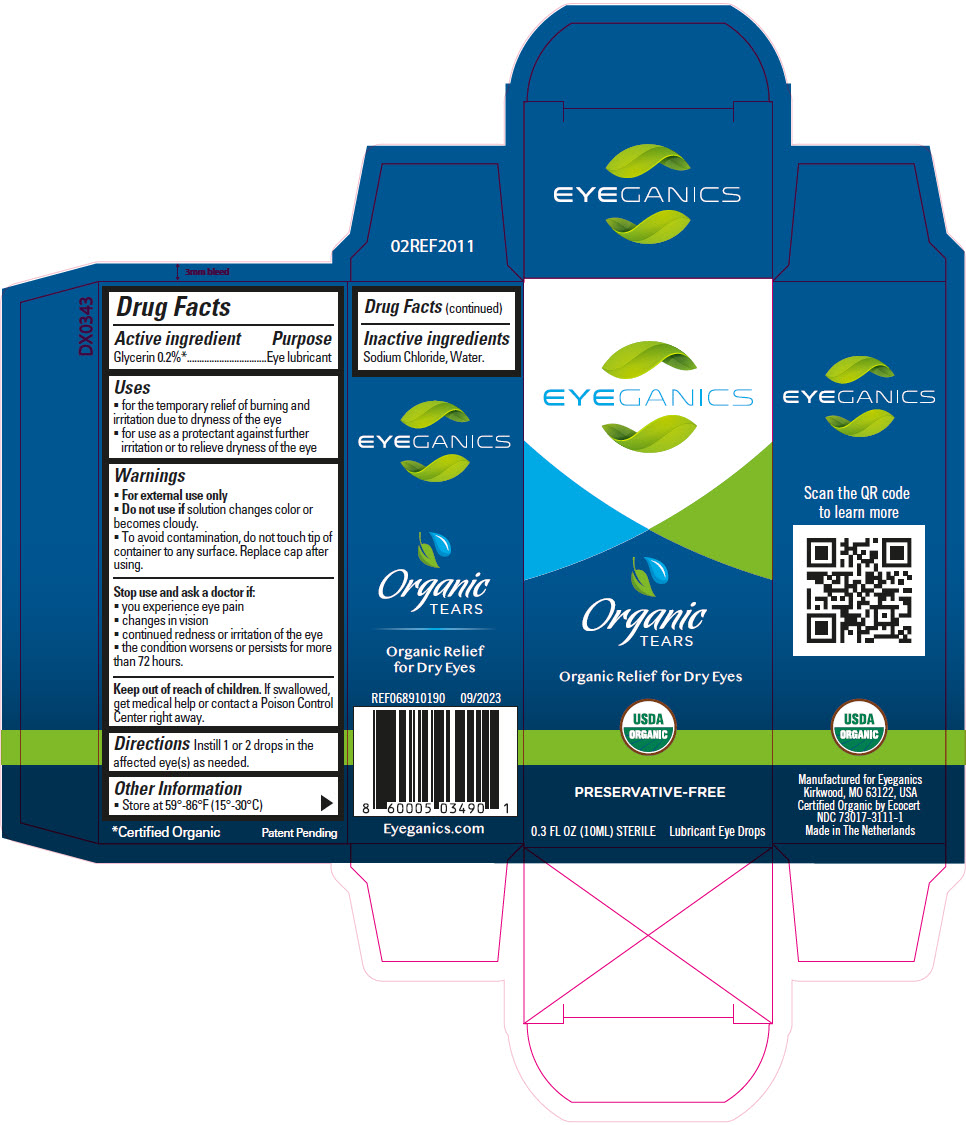 DRUG LABEL: Eyeganics Organic Tears
NDC: 73017-3111 | Form: SOLUTION/ DROPS
Manufacturer: Eyeganics LLC
Category: otc | Type: HUMAN OTC DRUG LABEL
Date: 20231013

ACTIVE INGREDIENTS: Glycerin 2 mg/1 mL
INACTIVE INGREDIENTS: Sodium Chloride; Water

Eyeganics Organic Tears

Drug Facts

Active ingredient

Glycerin 0.2% [Certified Organic]

Purpose

Eye lubricant

Uses

- for the temporary relief of burning and irritation due to dryness of the eye
- for use as a protectant against further irritation or to relieve dryness of the eye

Warnings

- For external use only

- Do not use if solution changes color or becomes cloudy.

WHEN USING

- To avoid contamination, do not touch tip of container to any surface. Replace cap after using.

Stop use and ask a doctor if:

- you experience eye pain
- changes in vision
- continued redness or irritation of the eye
- the condition worsens or persists for more than 72 hours.

Keep out of reach of children. If swallowed, get medical help or contact a Poison Control Center right away.

Directions

Instill 1 or 2 drops in the affected eye(s) as needed.

Other Information

- Store at 59°-86°F (15°-30°C).

Inactive ingredients

Sodium Chloride, Water.

PRINCIPAL DISPLAY PANEL - 10 ML Bottle Carton

EYEGANICS

Organic
TEARS

Organic Relief for Dry Eyes

USDA
ORGANIC

PRESERVATIVE-FREE

0.3 FL OZ (10ML) STERILE
Lubricant Eye Drops